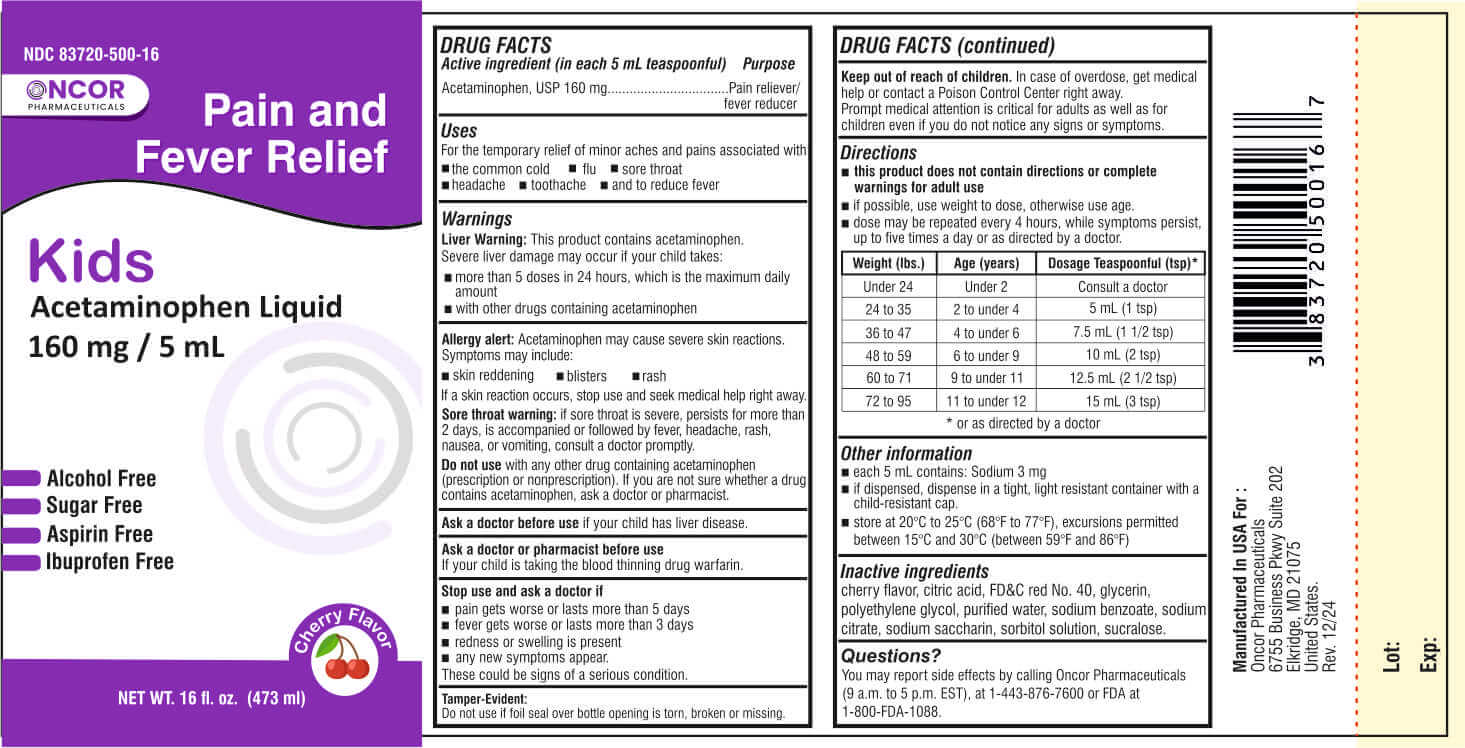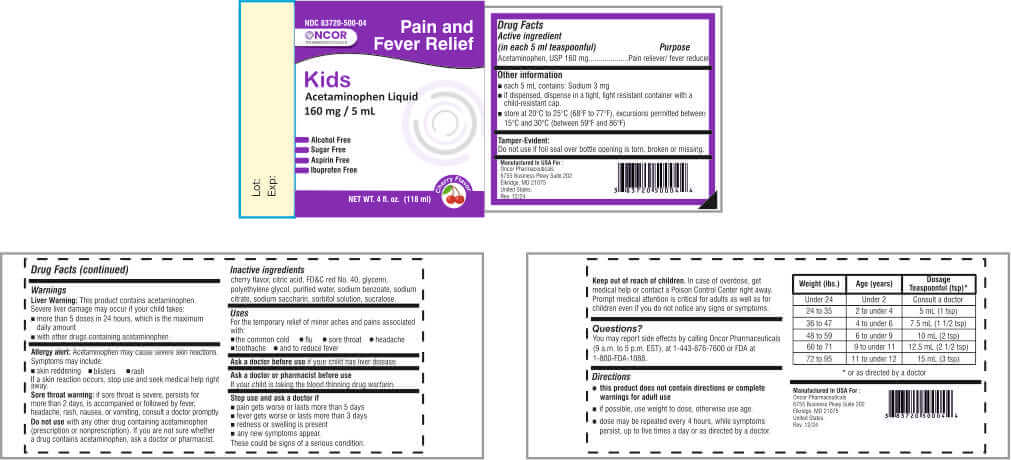 DRUG LABEL: Acetaminophen
NDC: 83720-500 | Form: LIQUID
Manufacturer: Oncor Pharmaceuticals
Category: otc | Type: HUMAN OTC DRUG LABEL
Date: 20250428

ACTIVE INGREDIENTS: ACETAMINOPHEN 160 mg/5 mL
INACTIVE INGREDIENTS: CITRIC ACID MONOHYDRATE; FD&C RED NO. 40; POLYETHYLENE GLYCOL, UNSPECIFIED; WATER; SORBITOL; SODIUM BENZOATE; SODIUM CITRATE, UNSPECIFIED FORM; SACCHARIN SODIUM

Acetaminophen

Drug Facts

Active ingredient (in each 5 mL teaspoonful)

Acetaminophen, USP 160 mg

Purpose

Pain reliever/Fever reducer

Uses

For the temporary relief of minor aches and pains associated with:

• the common cold
• flu
• sore throat
• headache
• toothache
• and to reduce fever

Warnings:

Liver warning: This product contains acetaminophen. Severe liver damage may occur if your child takes:

• more than 5 doses in 24 hours, which is the maximum daily amount

• with other drugs containing acetaminophen

Allergy alert: Acetaminophen may cause severe skin reactions.
Symptoms may include:
• skin reddening • blisters • rash

If a skin reaction occurs, stop use and seek medical help right away.

Sore throat warning: if sore throat is severe, persists for more than 2 days, is accompanied or followed by fever, headache, rash, nausea, or vomiting, consult a doctor promptly.

Do not use with any other drug containing acetaminophen (prescription or nonprescription). If you are not sure whether a drug contains acetaminophen, ask a doctor or pharmacist.

Ask a doctor before use if your child has liver disease.

Ask a doctor or pharmacist before use if your child is taking the blood thinning drug warfarin.

Stop use and ask a doctor if• pain gets worse or lasts more than 5 days

- pain gets worse or lasts more than 5 day.
- fever gets worse or lasts more than 3 days
- redness or swelling is present.
- any new symotom appear.

These could be signs of a serious condition.

Keep out of reach of children.In case of overdose, get medical help or contact a Poison Control Center right away. Prompt medical attention is critical for adults as well as for children even if you do not notice any signs or symptoms.

Directions

- this product does not contain directions or complete warnings for adult use
- Use only the enclosed dosing cup designed for use with this product.
- if possible, use weight to dose, otherwise use age.
- dose may be repeated every 4 hours, while symptoms persist, up to five times a day or as directed by a doctor.

Weight (lbs.) | Age (years) | Dosage Teaspoonful (tsp)*
Under 24 | Under 2 | Consult a doctor
24 to 35 | 2 to under 4 | 5 mL (1 tsp)
36 to 47 | 4 to under 6 | 7.5 mL (1 1/2 tsp)
48 to 59 | 6 to under 9 | 10 mL (2 tsp)
60 to 71 | 9 to under 11 | 12.5 mL (2 1/2 tsp)
72 to 95 | 11 to under 12 | 15 mL (3 tsp)

* or as directed by a doctor

Other information

- Each 5 mL contains: Sodium 3 mg
- If dispensed, dispense in a tight, light resistant container with a child-resistant cap.
- Store at 20°C to 25°C (68°F to 77°F), excursions permitted between 15°C and 30°C (between 59°F and 86°F)

Inactive ingredients

Cherry Flavor, Citric Acid, FD&C Red No. 40, Glycerin, Polyethylene Glycol, Purified Water, Sodium Benzoate, Sodium Citrate, Sodium Saccharin, Sorbitol Solution, Sucralose.

Questions?

You may report side effects by calling Oncor Pharmaceuticals (9 a.m. to 5 p.m. EST), at 1-443-876-7600 or FDA at 1-800-FDA-1088.

Tamper-Evident:
Do not use if foil seal over bottle opening is torn, broken, or missing.

Manufactured In USA For :
Oncor Pharmaceuticals
6755 Business Pkwy Suite 202
Elkridge, MD 21075
United States.

Rev. 01/2024

PRINCIPAL DISPLAY PANEL

ONCOR PHARMACEUTICALS

NDC 83720- 500-16

Pain and
Fever Relief

kids

Acetaminophen
Liquid 160 mg / 5 mL

Alcohol Free

Sugar Free

Aspirin Free

Ibuprofen Free

Cherry Flavor

16 fl. oz. - 473 mL

ONCOR PHARMACEUTICALS

NDC 83720- 500-16

Pain and
Fever Relief

kids

Acetaminophen
Liquid 160 mg / 5 mL

Alcohol Free

Sugar Free

Aspirin Free

Ibuprofen Free

Cherry Flavor

4 fl. oz. - 118 mL